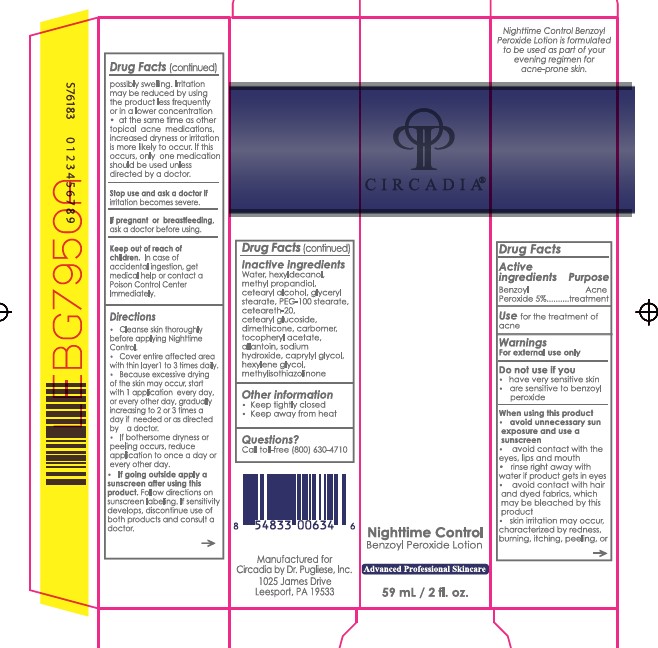 DRUG LABEL: Nighttime Control
NDC: 76458-333 | Form: LOTION
Manufacturer: Circadia by Dr Pugliese, Inc.
Category: otc | Type: HUMAN OTC DRUG LABEL
Date: 20231215

ACTIVE INGREDIENTS: BENZOYL PEROXIDE 50 mg/1 mL
INACTIVE INGREDIENTS: CARBOMER INTERPOLYMER TYPE A (ALLYL SUCROSE CROSSLINKED); WATER; HEXYLDECANOL; METHYLPROPANEDIOL; CETOSTEARYL ALCOHOL; GLYCERYL 1-STEARATE; PEG-100 STEARATE; CETEARYL GLUCOSIDE; DIMETHICONE; .ALPHA.-TOCOPHEROL ACETATE; ALLANTOIN; CAPRYLYL GLYCOL; HEXYLENE GLYCOL; METHYLISOTHIAZOLINONE; SODIUM HYDROXIDE; POLYOXYL 20 CETOSTEARYL ETHER

Nighttime Control

Active ingredient

Benzoyl Peroxide 5%

Purpose

Acne Treatment

Uses

for the treatment of acne

Warnings

For external use only

Do not use if you

When using this product

- have very sensitive skin
- are sensitive to benzoyl peroxide

- avoid unnecessary sun exposure and use a sunscreen
- avoid contact with the eyes, lips and mouth
- avoid contact with hair and dyed fabrics, which may be bleached by this product
- skin irritation may occur, characterized by redness, burning, itching, peeling, or possibly swelling. Irritation may be reduced by using the product less frequently or in a lower concentration
- at the same time as other topical acne medications, increased dryness or irritation is more likely to occur. If this occurs, only one medication should be used unless directed by a doctor.

Stop use and ask a doctor

if irritation becomes severe.

ask a doctor before using. If pregnant or breastfeeding,

Keep Out of Reach of Children

In case of accidental ingestion, get medical help or contact a Poison Control Center Immediately.

Directions

- Cleanse skin thoroughly before applying Nighttime Control.
- Cover entire affected area with a thin layer 1 to 3 times daily.
- Because excessive drying of the skin may occur, start with 1 application every day, or every other day, gradually increasing to 2 or 3 times a day if needed or as directed by a doctor.
- If bothersome dryness or peeling occurs, reduce application to once a day or every other day.
- Follow directions on sunscreen labeling. If sensitivity develops, discontinue use of both products and consult a doctor. If going outside apply a sunscreen after using this product.

Inactive ingredients

Water, hexyldecanol, methyl propanediol, cetearyl alcohol, glyceryl stearate, PEG-100 stearate, cetereth-20, cetearyl glucoside, dimethicone, carbomer, tocopheryl acetate, allantoin, sodium hydroxide, caprylyl glycol, hexylene glycol, methylisothiazolinone

Other Information

- Keep tightly closed
- Keep away from heat

Questions?

Call toll-free (800) 630-4710

Package/Label Principal Display Panel

Nighttime Control Benzoyl Peroxide Lotion

Advanced Professional Skincare

2 fl oz (59 ml)

Circadia by Dr. Pugliese, Inc. 8371 Route 183 Bethel, PA 19507 Circadia.com